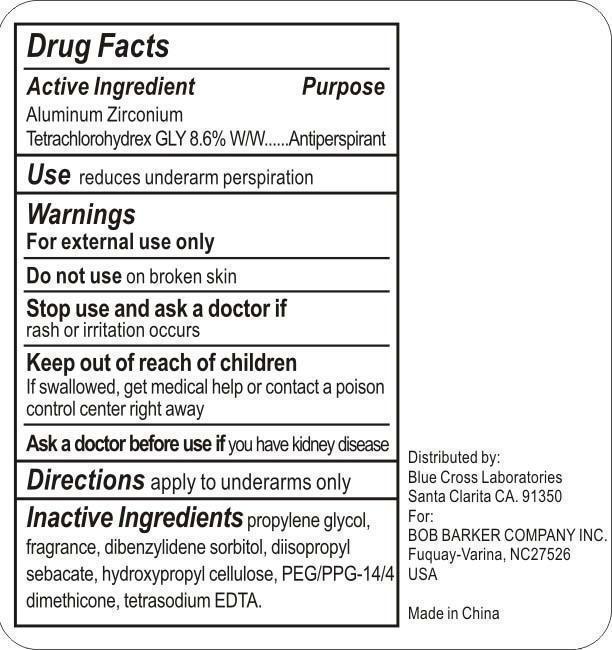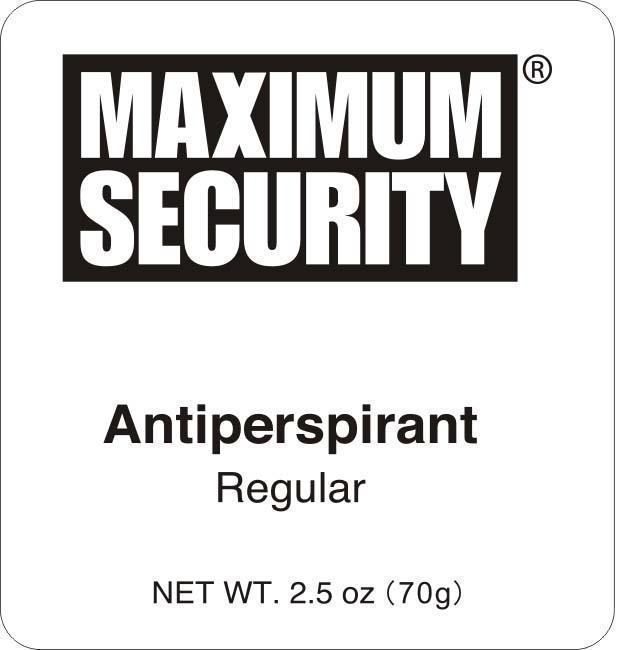 DRUG LABEL: Antiperspirant
NDC: 22431-641 | Form: STICK
Manufacturer: Blue Cross Labs
Category: otc | Type: HUMAN OTC DRUG LABEL
Date: 20181220

ACTIVE INGREDIENTS: ALUMINUM ZIRCONIUM TETRACHLOROHYDREX GLY 6.02 g/70 g
INACTIVE INGREDIENTS: PROPYLENE GLYCOL; DIISOPROPYL SEBACATE; HYDROXYPROPYL CELLULOSE

Maximum Security Antiperspirant

Active ingredient Purpose

Aluminum Zirconium tetrachlorohydrex Gly 8.6% W/W Antiperspirant

PURPOSE

Use reduces underarm perspiration

Keep out of reach of children

If swallowed get medical help or contact a poison control center right away.

Stop use and ask a doctor if rash or irritation occurs.

Warnings
For external use only
Do not use on broken skin

DOSAGE AND ADMINISTRATION

Directions apply to underarms only

Inactive ingredients

Propylene glycol, fragrance, dibenzylidene sorbitol, diisopropyl sebacate, hydroxypropyl cellulose, PEG/PPG-14/4 dimethicone, tetrasodium EDTA.

PACKAGE LABEL

Maximum Security

Antiperspirant

Regular

Net WT. 2.5 oz (70g)